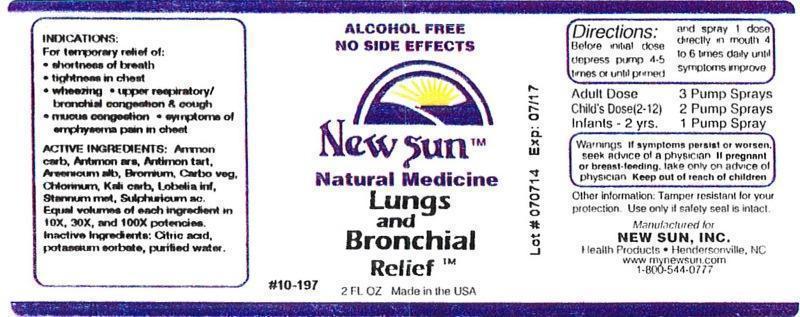 DRUG LABEL: Lungs and Bronchial Relief
NDC: 66579-0067 | Form: LIQUID
Manufacturer: New Sun Inc.
Category: homeopathic | Type: HUMAN OTC DRUG LABEL
Date: 20140717

ACTIVE INGREDIENTS: AMMONIUM CARBONATE 10 [hp_X]/59 mL; ANTIMONY ARSENATE 10 [hp_X]/59 mL; ANTIMONY POTASSIUM TARTRATE 10 [hp_X]/59 mL; ARSENIC TRIOXIDE 10 [hp_X]/59 mL; BROMINE 10 [hp_X]/59 mL; ACTIVATED CHARCOAL 10 [hp_X]/59 mL; CHLORINE 10 [hp_X]/59 mL; POTASSIUM CARBONATE 10 [hp_X]/59 mL; LOBELIA INFLATA 10 [hp_X]/59 mL; TIN 10 [hp_X]/59 mL; SULFURIC ACID 10 [hp_X]/59 mL
INACTIVE INGREDIENTS: CITRIC ACID MONOHYDRATE; POTASSIUM SORBATE; WATER

Lungs and Bronchial Relief

DOSAGE AND ADMINISTRATION

Directions: Before initial dose depress pump 4-5 times or until primed and spray 1 dose directly in mouth 4 to 6 times daily until symptoms improve.

Adult Dose: 3 Pump Sprays

Child's Dose (2-12): 2 Pump Sprays

Infants - 2 yrs: 1 Pump Spray

WARNINGS

Warnings: If symptoms persist or worsen, seek advice of physician. If pregnant or breast-feeding, take only on advice of physician.

Keep out of reach of children.

Other information: Tamper resistant for your protection. Use only if safety seal is intact.

PURPOSE

Indications: For temporary relief of: •shortness of breath •tightness in chest •wheezing •upper respiratory/bronchial congestion & cough •mucus congestion •symptoms of emphysema pain in chest

ACTIVE INGREDIENT

Active Ingredients: Ammonium carbonicum, Antimonium arsenicicum, Antimonium tartaricum, Arsenicum album, Bromium, Carbo vegetabilis, Chlorinum, Kali carbonicum, Lobelia inflata, Stannum metallicum, Sulphuricum acidum. Equal volumes of each ingredient in 10X, 30X, and 100X potencies.

Inactive Ingredient: Citric acid, potassium sorbate, purified water.

Indications: For temporary relief of:

- shortness of breath
- tightness in chest
- wheezing
- upper respiratory/bronchial congestion & cough
- mucus congestion
- symptoms of emphysema pain in chest